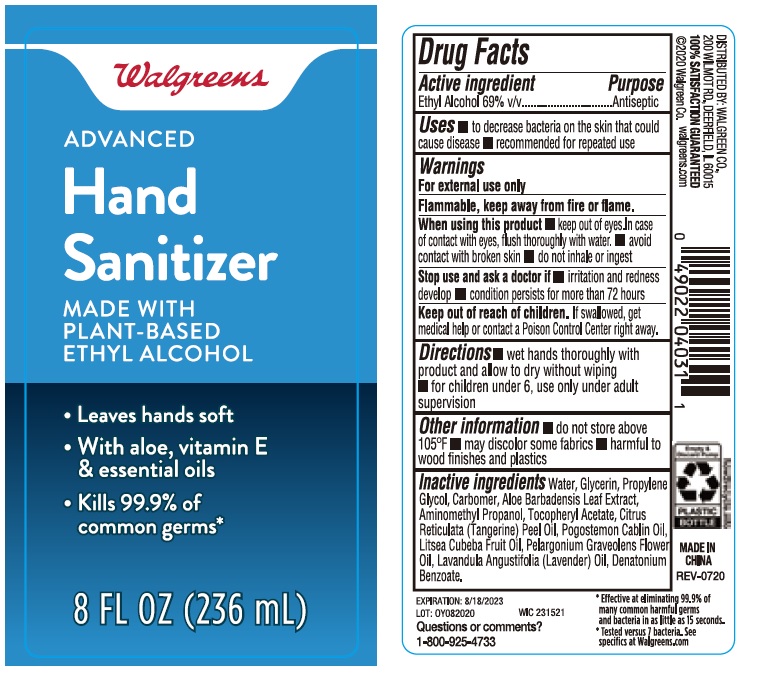 DRUG LABEL: Walgreens Advanced Hand Sanitizer Made with Plant-Based Ethyl Alcohol
NDC: 0363-9005 | Form: GEL
Manufacturer: Walgreen Company
Category: otc | Type: HUMAN OTC DRUG LABEL
Date: 20200814

ACTIVE INGREDIENTS: ALCOHOL 69 mL/100 mL
INACTIVE INGREDIENTS: PROPYLENE GLYCOL; DENATONIUM BENZOATE; CARBOMER HOMOPOLYMER, UNSPECIFIED TYPE; ALOE VERA LEAF; AMINOMETHYLPROPANOL; PELARGONIUM GRAVEOLENS FLOWER OIL; WATER; GLYCERIN; .ALPHA.-TOCOPHEROL ACETATE; LITSEA OIL; POGOSTEMON CABLIN LEAF OIL; LAVENDER OIL; MANDARIN OIL

Walgreens Advanced Hand Sanitizer Made with Plant-Based Ethyl Alcohol

Active ingredient

Ethyl alcohol 69% v/v

Purpose

Antiseptic

Uses

- to decrease bacteria on the skin that could cause disease
- recommended for repeated use

Warnings

For external use only

Flammable, keep away from fire or flame.

When using this product

- keep out of eyes. In case of contact with eyes, flush thoroughly with water.
- avoid contact with broken skin
- do not inhale or ingest

Stop use and ask a doctor if

- irritation and redness develop
- condition persists for more than 72 hours

Keep out of reach of children.

If swallowed, get medical help or contact a Poison Control Center right away.

Directions

- wet hands thoroughly with product and allow to dry without wiping
- for children under 6, use only under adult supervision

Other information

- do not store above 105F
- may discolor some fabrics
- harmful to wood finishes and plastics

Inactive ingredients

Water, Glycerin, Propylene Glycol, Carbomer, Aloe Barbadensis Leaf Extract, Aminomethyl Propanol, Tocopheryl Acetate, Citrus Reticulata (Tangerine) Peel Oil, Pogostemon Cablin Oil, Litsea Cubeba Fruit Oil, Pelargonium Graveolens Flower Oil, Lavandula Angustifolia (Lavender) Oil, Denatonium Benzoate.

Company Information

DISTRIBUTED BY: WALGREEN CO.,

200 WILMOT RD., DEERFIELD, IL 60015

Product Packaging

Walgreens

ADVANCED

Hand

Sanitizer

MADE WITH

PLANT-BASED

ETHYL ALCOHOL

- Leaves hands soft
- With aloe, vitamin E & essential oils
- Kills 99.9% of common germs

8 FL OZ (236 mL)